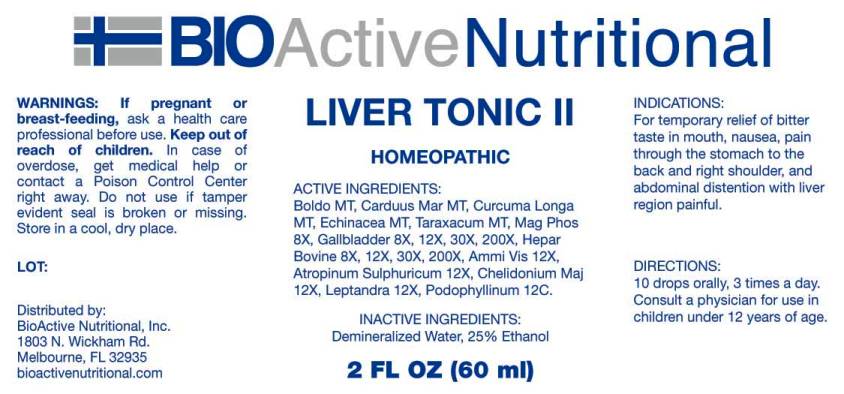 DRUG LABEL: Liver Tonic
NDC: 43857-0328 | Form: LIQUID
Manufacturer: BioActive Nutritional, Inc.
Category: homeopathic | Type: HUMAN OTC DRUG LABEL
Date: 20170210

ACTIVE INGREDIENTS: PEUMUS BOLDUS LEAF 1 [hp_X]/1 mL; MILK THISTLE 1 [hp_X]/1 mL; TURMERIC 1 [hp_X]/1 mL; ECHINACEA ANGUSTIFOLIA 1 [hp_X]/1 mL; TARAXACUM OFFICINALE 1 [hp_X]/1 mL; MAGNESIUM PHOSPHATE, DIBASIC TRIHYDRATE 8 [hp_X]/1 mL; BOS TAURUS GALLBLADDER 8 [hp_X]/1 mL; BEEF LIVER 8 [hp_X]/1 mL; AMMI VISNAGA FRUIT 12 [hp_X]/1 mL; ATROPINE SULFATE 12 [hp_X]/1 mL; CHELIDONIUM MAJUS 12 [hp_X]/1 mL; VERONICASTRUM VIRGINICUM ROOT 12 [hp_X]/1 mL; PODOPHYLLUM RESIN 12 [hp_C]/1 mL
INACTIVE INGREDIENTS: WATER; ALCOHOL

Drug Facts:

ACTIVE INGREDIENTS:

Boldo MT, Carduus Marianus MT, Curcuma Longa MT, Echinacea (Angustifolia) MT, Taraxacum Officinale MT, Magnesia Phosphorica 8X, Gallbladder (bovine) 8X, 12X, 30X, 200X, Hepar Bovine 8X, 12X, 30X, 200X, Ammi Visnaga 12X, Atropinum Sulphuricum 12X, Chelidonium Majus 12X, Leptandra Virginica 12X, Podophyllinum 12C.

INDICATIONS:

For temporary relief of bitter taste in mouth, nausea, pain through the stomach to the back and right shoulder, and abdominal distention with liver region painful.

WARNINGS:

If pregnant or breast-feeding, ask a health care professional before use.

Keep out of reach of children. In case of overdose, get medical help or contact a Poison Control Center right away.

Do not use if tamper evident seal is broken or missing.

Store in cool, dry place.

Keep out of reach of children. In case of overdose, get medical help or contact a Poison Control Center right away.

DIRECTIONS:

10 drops orally, 3 times a day. Consult a physician for use in children under 12 years of age.

INDICATIONS:

For temporary relief of bitter taste in mouth, nausea, pain through the stomach to the back and right shoulder, and abdominal distention with liver region painful.

INACTIVE INGREDIENTS:

Demineralized Water, 25% Ethanol.

QUESTIONS:

Distributed by:
BioActive Nutritional, Inc.
1803 N. Wickham Rd.
Melbourne, FL 32935
bioactivenutritional.com

PACKAGE LABEL DISPLAY:

BIOActive Nutritional

LIVER TONIC II

HOMEOPATHIC

2 FL OZ (60 ml)